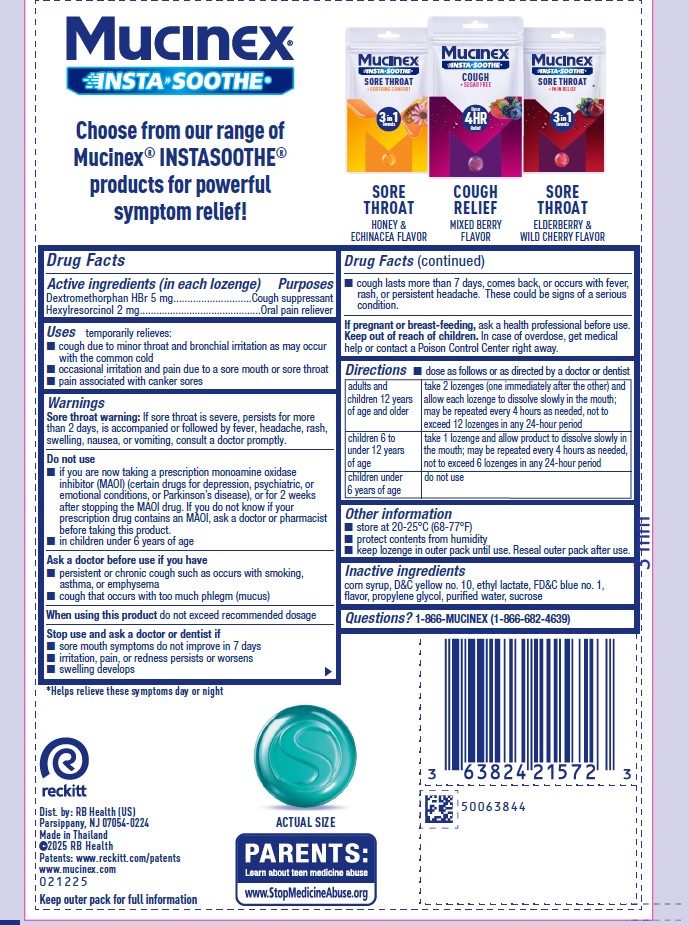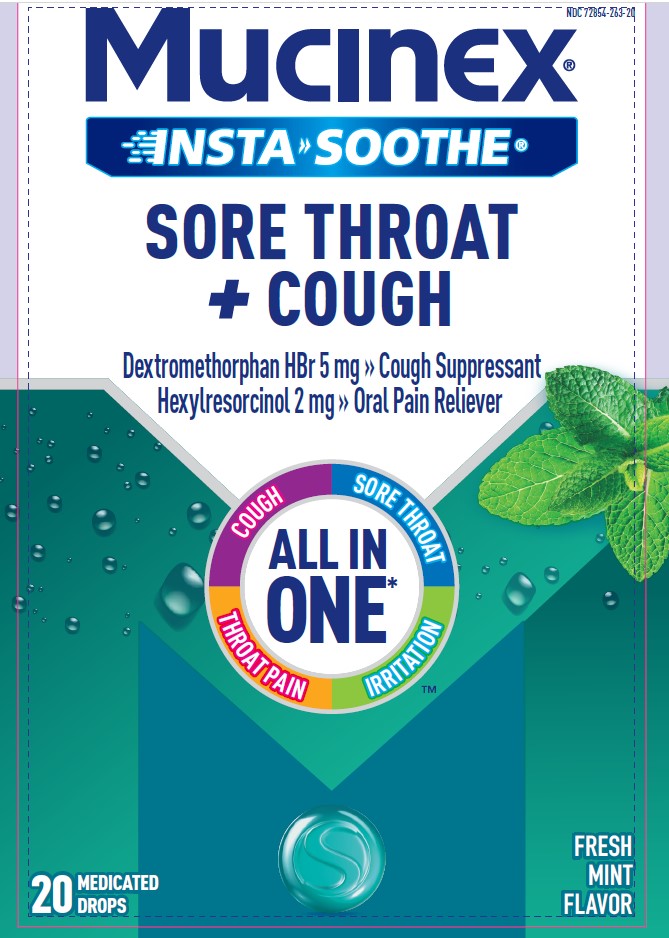 DRUG LABEL: MUCINEX INSTASOOTHE
NDC: 72854-263 | Form: LOZENGE
Manufacturer: RB Health (US) LLC
Category: otc | Type: HUMAN OTC DRUG LABEL
Date: 20250408

ACTIVE INGREDIENTS: DEXTROMETHORPHAN HYDROBROMIDE 5 mg/1 1; HEXYLRESORCINOL 2 mg/1 1
INACTIVE INGREDIENTS: CORN SYRUP; D&C YELLOW NO. 10; ETHYL LACTATE; FD&C BLUE NO. 1; PROPYLENE GLYCOL; SUCROSE; WATER

MUCINEX® INSTASOOTHE™
SORE THROAT PLUS COUGH RELIEF

Drug Facts

Active ingredients (in each lozenge)
Dextromethorphan HBr 5 mg
Hexylresorcinol 2 mg

PURPOSE

Active ingredients (in each lozenge) | Purposes
Dextromethorphan HBr 5 mg | Cough suppressant
Hexylresorcinol 2 mg | Oral pain reliever

Uses

temporarily relieves

- cough due to minor throat and bronchial irritation as may occur with the common cold
- occasional irritation and pain due to a sore mouth or sore throat
- pain associated with canker sores

Warnings

Sore throat warning

If sore throat is severe, persists for more than 2 days, is accompanied or followed by fever, headache, rash, swelling, nausea, or vomiting, consult a doctor promptly.

Do not use

- if you are now taking a prescription monoamine oxidase inhibitor (MAOI) (certain drugs for depression, psychiatric, or emotional conditions, or Parkinson's disease), or for 2 weeks after stopping the MAOI drug. If you do not know if your prescription drug contains an MAOI, ask a doctor or pharmacist before taking this product.
- in children under 6 years of age

When using this productdo not exceed recommended dosage

Ask a doctor before use if you have

- persistent or chronic cough such as occurs with smoking, asthma, or emphysema
- cough that occurs with too much phlegm (mucus)

Stop use and ask a doctor or dentist if

- sore mouth symptoms do not improve in 7 days
- irritation, pain, or redness persists or worsens
- swelling develops
- cough lasts more than 7 days, comes back, or occurs with fever, rash, or persistent headache. These could be signs of a serious condition.

PREGNANCY OR BREAST FEEDING

If pregnant or breast-feeding,ask a health professional before use.

Keep out of reach of children.In case of overdose, get medical help or contact a Poison Control Center right away.

Directions

dose as follows or as directed by a doctor or dentist

adults and children 12 years of age and older | take 2 lozenges (one immediately after the other) and allow each lozenge to dissolve slowly in the mouth; may be repeated every 4 hours as needed, not to exceed 12 lozenges in any 24-hour period
children 6 to under 12 years of age | take 1 lozenge and allow product to dissolve slowly in the mouth; may be repeated every 4 hours as needed, not to exceed 6 lozenges in any 24-hour period
children under 6 years of age | do not use

Other information

- store at 20-25°C (68-77°F)
- protect contents from humidity
- keep lozenge in outer pack until use. Reseal outer pack after use.

Inactive ingredients

corn syrup, D&C yellow no. 10, ethyl lactate, FD&C blue no. 1, flavor, propylene glycol, purified water, sucrose.

Questions?

1-866-MUCINEX (1-866-682-4639)

Dist. by: RB Health (US)
Parsippany,
NJ 07054-0224
Made in Thailand

PRINCIPAL DISPLAY PANEL - 20 Drop Pouch Bag

NDC 72854-263-20

Mucinex®
INSTASOOTHE™

SORE THROAT
+ COUGH RELIEF

Dextromethorphan HBr 5.0 mg | Cough Suppressant
Hexylresorcinol 2.0 mg | Oral Pain Reliever

3 IN 1 FORMULA

✔ Up to 4 Hours Cough Relief
✔ Cooling Comfort
✔ Fast Acting

See back
panel for
actual size

Winter Mint Flavor

20 MEDICATED DROPS